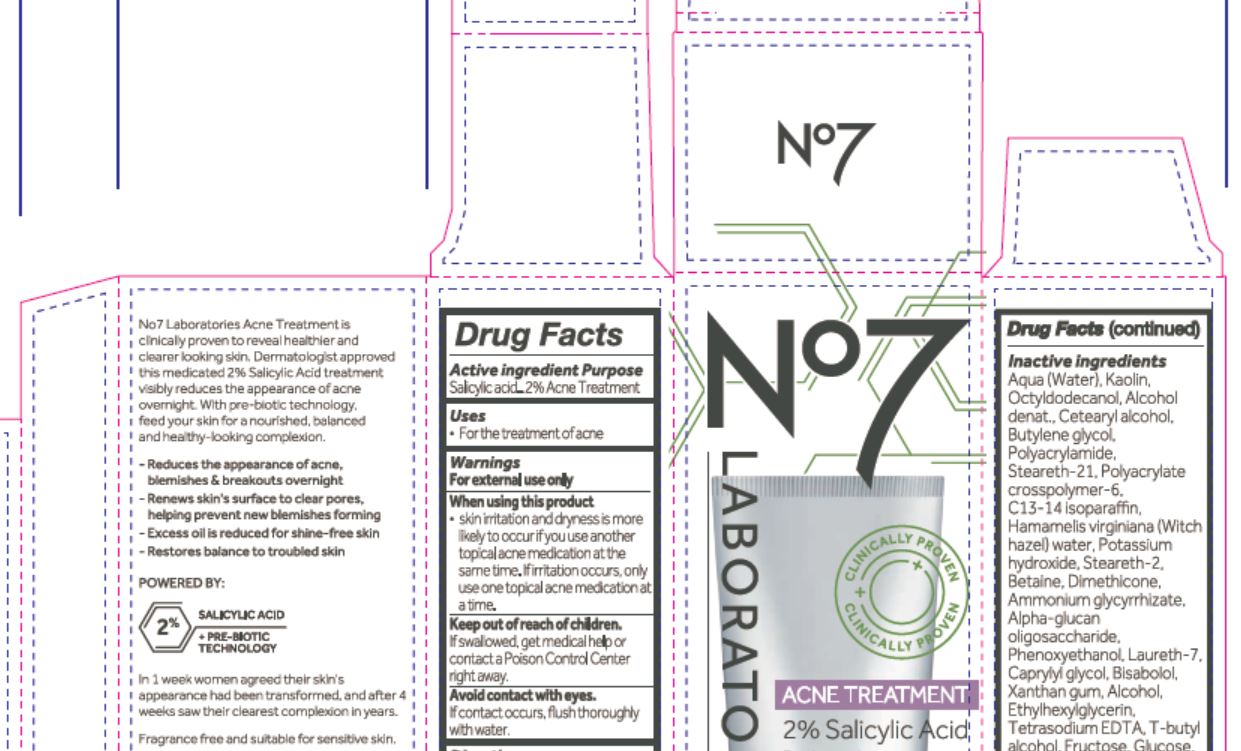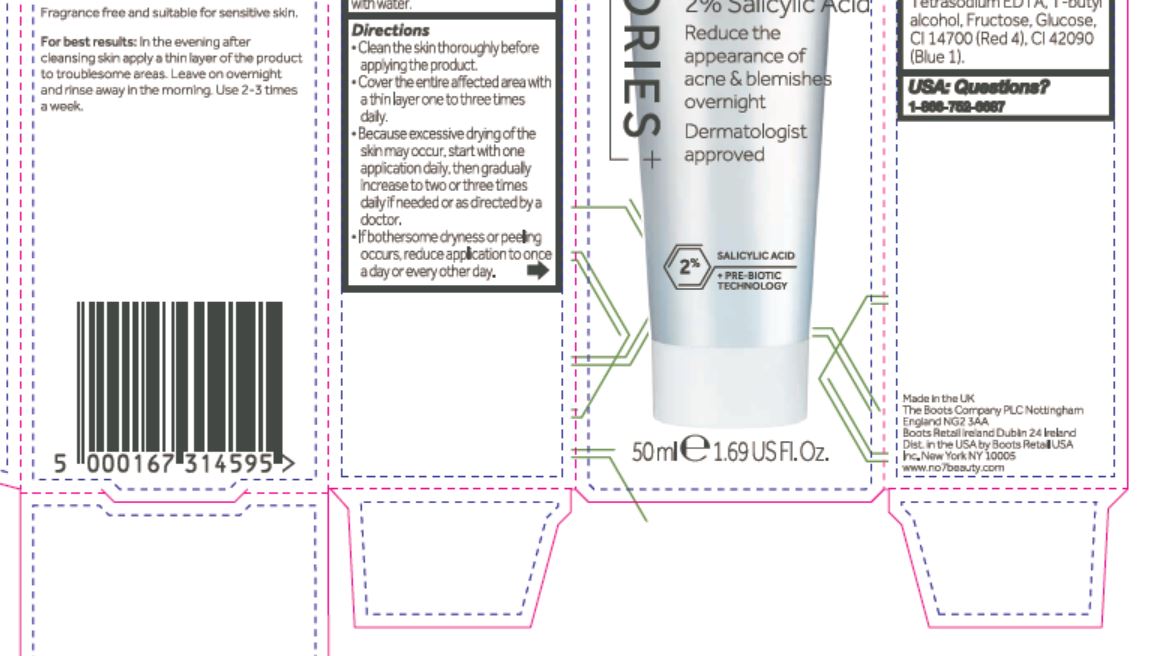 DRUG LABEL: No7 Laboratories Acne Treatment
NDC: 11489-176 | Form: LIQUID
Manufacturer: BCM Ltd
Category: otc | Type: HUMAN OTC DRUG LABEL
Date: 20201104

ACTIVE INGREDIENTS: SALICYLIC ACID 1 g/50 g
INACTIVE INGREDIENTS: WATER; KAOLIN; OCTYLDODECANOL; ALCOHOL; CETOSTEARYL ALCOHOL; BUTYLENE GLYCOL; POLYACRYLAMIDE (10000 MW); STEARETH-21; TRIMETHYLOLPROPANE TRIACRYLATE; C13-14 ISOPARAFFIN; HAMAMELIS VIRGINIANA LEAF WATER; POTASSIUM HYDROXIDE; STEARETH-2; BETAINE; DIMETHICONE; AMMONIUM GLYCYRRHIZATE; .ALPHA.-GLUCAN OLIGOSACCHARIDE; PHENOXYETHANOL; LAURETH-7; CAPRYLYL GLYCOL; BISABOLOL OXIDE A; XANTHAN GUM; ETHYLHEXYLGLYCERIN; ETIDRONATE TETRASODIUM; TERT-BUTYL ALCOHOL; FRUCTOSE; DEXTROSE

No7 Laboratories Acne Treatment

Active Ingredients

Active ingredient Purpose

Salicylic acid Acne Treatment

Dosage

2%

Uses

For the treatment of acne

Warnings

For external use only

When using this product

skin irritation and dryess is more likely to occur if you use anohter topical acne medication at the same time. If irritation occurs, only use on topical acne medication at a time.

Avoid contact with eyes.

If contact occurs, flush thoroughly with water.

Keep out of reach of children

If swallowed, get medical help or contact a Poison Control Center right away.

Directions

Clean the skin thoroughly before applying the product.

Cover the entire affected area with a thin layer one to three times daily.

Because excessive drying of the skin may occur, start with one application daily, then gradually increase to two or three times daily if needed or as directed by a doctor.

If bothersome dryness or peeling occurs, reduce application to once a day or every other day.

Inactive ingredients

Aqua (Water), Kaolin, Octyldodecanol, Alcohol denat., Cetearyl alcohol, Butylene glycol, Polyacrylamide, Steareth-21, Polyacrylate crosspolymer-6, C13-14 isoparaffin, Hamamelis virginiana (Witch hazel) water, Potassium hydroxide, Steareth-2, betaine, Dimethicon, Ammonium glycyrrhizate, Alpha-glucan oligosaccharide, Phenoxyethanol, Laureth-7, Caprylyl glycol, Bisabolol, Xanthan gum, Alcohol, Exylhexylglycerin, Tetrasodium EDTA, T-butyl alcohol, Fructose, Glucose, CI 14700 (Red 4), CI 42090 (Blue 1).

PATIENT COUNSELING INFORMATION

Made in the UK

The Boots Company PLC

Nottingham England NG2 3AA

Dist. in the USA by Boots Retail USA Inc.

New York NY 10005

Made in the UK

www.no7beauty.com

Questions

USA: Questions? 1-866-752-6687

Description

No7

LABORATORIES

CLINICALLY PROVEN

CLINICALLY PROVEN

ACNE TREATMENT

2% Salicylic Acid

Reduce the appearance of acne & blemishes overnight

Dermatologist approved

2% SALICYLIC ACID

+ PRE-BIOTIC TECHNOLOGY

50 ml e 1.69 US Fl. Oz.

No7 Laboratories Acne Treatment is clinically proven to receal healthier and clearer looking skin. Dermatologist approved this medicated 2% Salicylic Acid treatment visibly reduces the appearance of acne overnight. With pre-biotic technology, feed your skin for a nourished, blanaced and health-looking complexion.

- Reduces the apperance of acne, blemishes & breakouts overnight

- Renews skin's surface to clear pores, helping to prevent new blemishes forming

- Excess oil is reduced for shine-free skin

- Restores balance to troubled skin

POWERED BY:

2% SALICYLIC ACID

+ PRE-BIOTIC TECHNOLOGY

In 1 week women agreed their skin's appearance had been transformed, and after 4 weeks saw their clearest complexion in years.

Fragrance free and suitable for sensitive skin.

For best results: In the evening after cleansing skin apply a thin layer of the product to troublesome area. Leav on overnight and rinse away in the morning. Use 2-3 times a week.

Carton